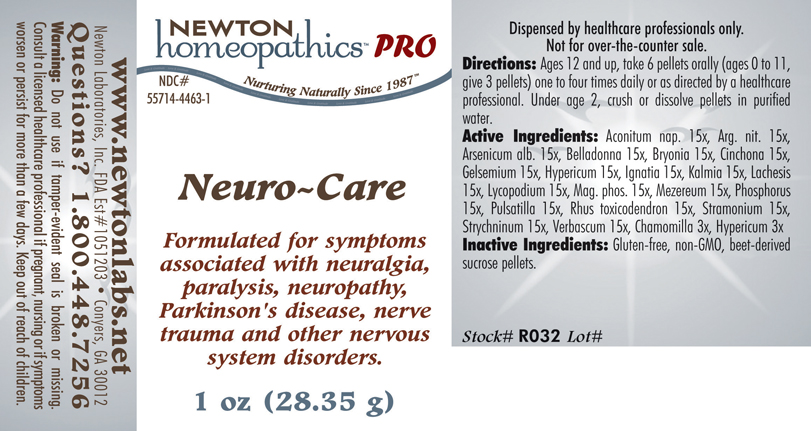 DRUG LABEL: Neuro - Care 
NDC: 55714-4463 | Form: PELLET
Manufacturer: Newton Laboratories, Inc.
Category: homeopathic | Type: HUMAN PRESCRIPTION DRUG LABEL
Date: 20110601

ACTIVE INGREDIENTS: Aconitum Napellus 15 [hp_X]/1 g; Silver Nitrate 15 [hp_X]/1 g; Arsenic Trioxide 15 [hp_X]/1 g; Atropa Belladonna 15 [hp_X]/1 g; Bryonia Alba Root 15 [hp_X]/1 g; Cinchona Officinalis Bark 15 [hp_X]/1 g; Gelsemium Sempervirens Root 15 [hp_X]/1 g; Hypericum Perforatum 15 [hp_X]/1 g; Strychnos Ignatii Seed 15 [hp_X]/1 g; Kalmia Latifolia Leaf 15 [hp_X]/1 g; Lachesis Muta Venom 15 [hp_X]/1 g; Lycopodium Clavatum Spore 15 [hp_X]/1 g; Magnesium Phosphate, Dibasic Trihydrate 15 [hp_X]/1 g; Daphne Mezereum Bark 15 [hp_X]/1 g; Phosphorus 15 [hp_X]/1 g; Pulsatilla Vulgaris 15 [hp_X]/1 g; Toxicodendron Pubescens Leaf 15 [hp_X]/1 g; Datura Stramonium 15 [hp_X]/1 g; Strychnine 15 [hp_X]/1 g; Verbascum Thapsus 15 [hp_X]/1 g; Matricaria Recutita 3 [hp_X]/1 g
INACTIVE INGREDIENTS: Sucrose

Neuro - Care

INDICATIONS & USAGE SECTION

Neuro - Care Formulated for symptoms associated with neuralgia, paralysis, neuropathy, Parkinson's disease, nerve trauma and other nervous system disorders.

DOSAGE & ADMINISTRATION SECTION

Directions: Ages 12 and up, take 6 pellets orally (ages 0 to 11, give 3 pellets) one to four times daily or as directed by a healthcare professional. Under age 2, crush or dissolve pellets in purified water.

ACTIVE INGREDIENT SECTION

Aconitum nap. 15x, Arg. nit. 15x, Arsenicum alb. 15x, Belladonna 15x, Bryonia 15x, Cinchona 15x, Gelsemium 15x, Hypericum 15x, Ignatia 15x, Kalmia 15x, Lachesis 15x, Lycopodium 15x, Mag. phos. 15x, Mezereum 15x, Phosphorus 15x, Pulsatilla 15x, Rhus toxicodendron 15x, Stramonium 15x, Strychninum 15x, Verbascum 15x, Chamomilla 3x, Hypericum 3x.

PURPOSE SECTION

Formulated for symptoms associated with neuralgia, paralysis, neuropathy, Parkinson's disease, nerve trauma and other nervous system disorders.

INACTIVE INGREDIENT SECTION

Inactive Ingredients: Gluten-free, non-GMO, beet-derived sucrose pellets.

QUESTIONS? SECTION

www.newtonlabs.net Newton Laboratories, Inc. FDA Est # 1051203 - Conyers, GA 30012
Questions? 1.800.448.7256

WARNINGS SECTION

Warning: Do not use if tamper - evident seal is broken or missing. Consult a licensed healthcare professional if pregnant, nursing or if symptoms worsen or persist for more than a few days. Keep out of reach of children.

PREGNANCY OR BREAST FEEDING SECTION

Consult a licensed healthcare professional if pregnant, nursing or if symptoms worsen or persist for more than a few days.

KEEP OUT OF REACH OF CHILDREN SECTION

Keep out of reach of children.